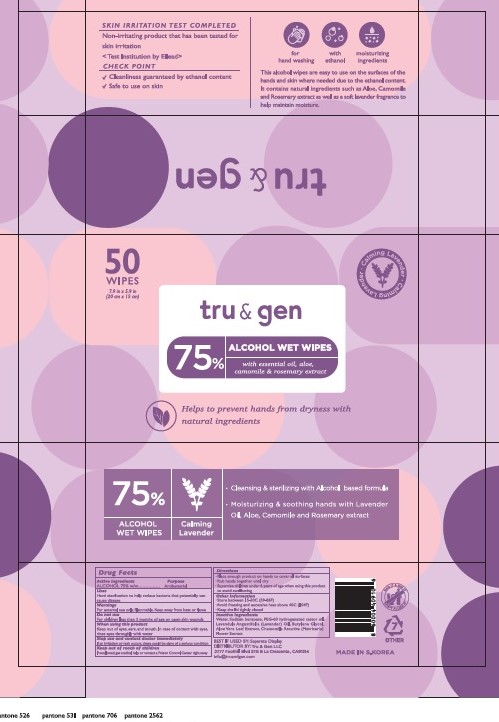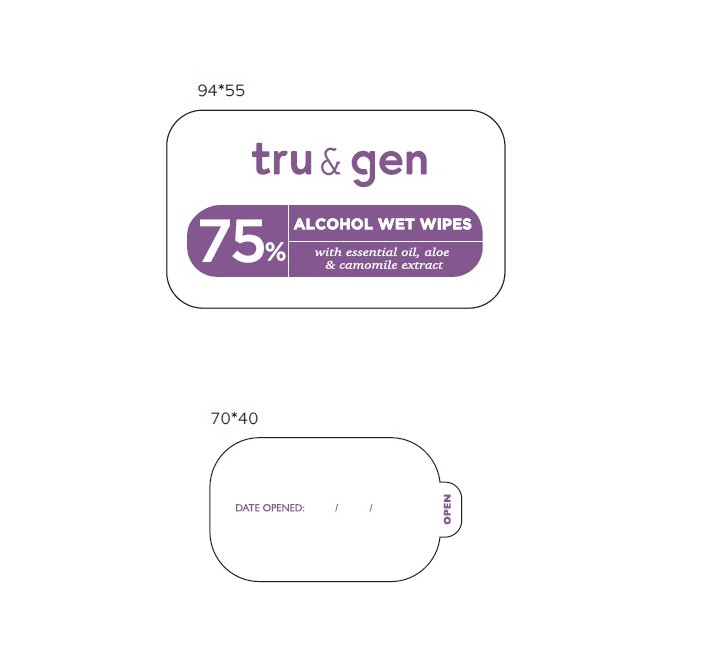 DRUG LABEL: TRU AND GEN 75% ALCOHOL WET WIPES
NDC: 80500-001 | Form: CLOTH
Manufacturer: TRU & GEN
Category: otc | Type: HUMAN OTC DRUG LABEL
Date: 20200908

ACTIVE INGREDIENTS: ALCOHOL 0.75 1/1 1
INACTIVE INGREDIENTS: MATRICARIA CHAMOMILLA; LAVENDER OIL; ALOE VERA LEAF; PEG-60 HYDROGENATED CASTOR OIL; SODIUM BENZOATE; WATER; BUTYLENE GLYCOL; HEXYLENE GLYCOL; ROSEMARY

TRU & GEN ALCOHOL WET WIPES

Active Ingredient

ALCOHOL ---- 75%

Purpose:

Antibacterial

Inactive Ingredients

Water, Sodium benzoate, PEG-60 Hydrogenated Castor Oil, Lavandual Angustifolia (Lavender) Oil, Butylene Glycol, Aloe Vera Leaf Extract, Chamomila Recutita (Matricaria) Flower Extract

Directions for Use

Place enough product on hands to cover all surfaces.

Rub hands together until dry

Supervise children under 6 years of age when using this product to avoid swallowing.

Warnings:

For External use only. Flammable. Keep away from heat or flame.

When using this product:

Keep out of eyes, ears, and mouth.

In case of contact with eyes, rinse eyes thoroughly with water.

Uses:

Hand Sterilization to help reduce bacteria that potentially can cause disease.

Keep Out of Reach of Children:

If swallowed, get medical help or contact a Poison Control Center right way.

Other Information:

Store between 15-30C (59-86F)

Avoid freezing and excessive heat above 40C (104F)

Keep the lid tightly closed

50 Wipes PDP, NDC: 80500-001-01

50 Wipes, NDC: 80500-001-01